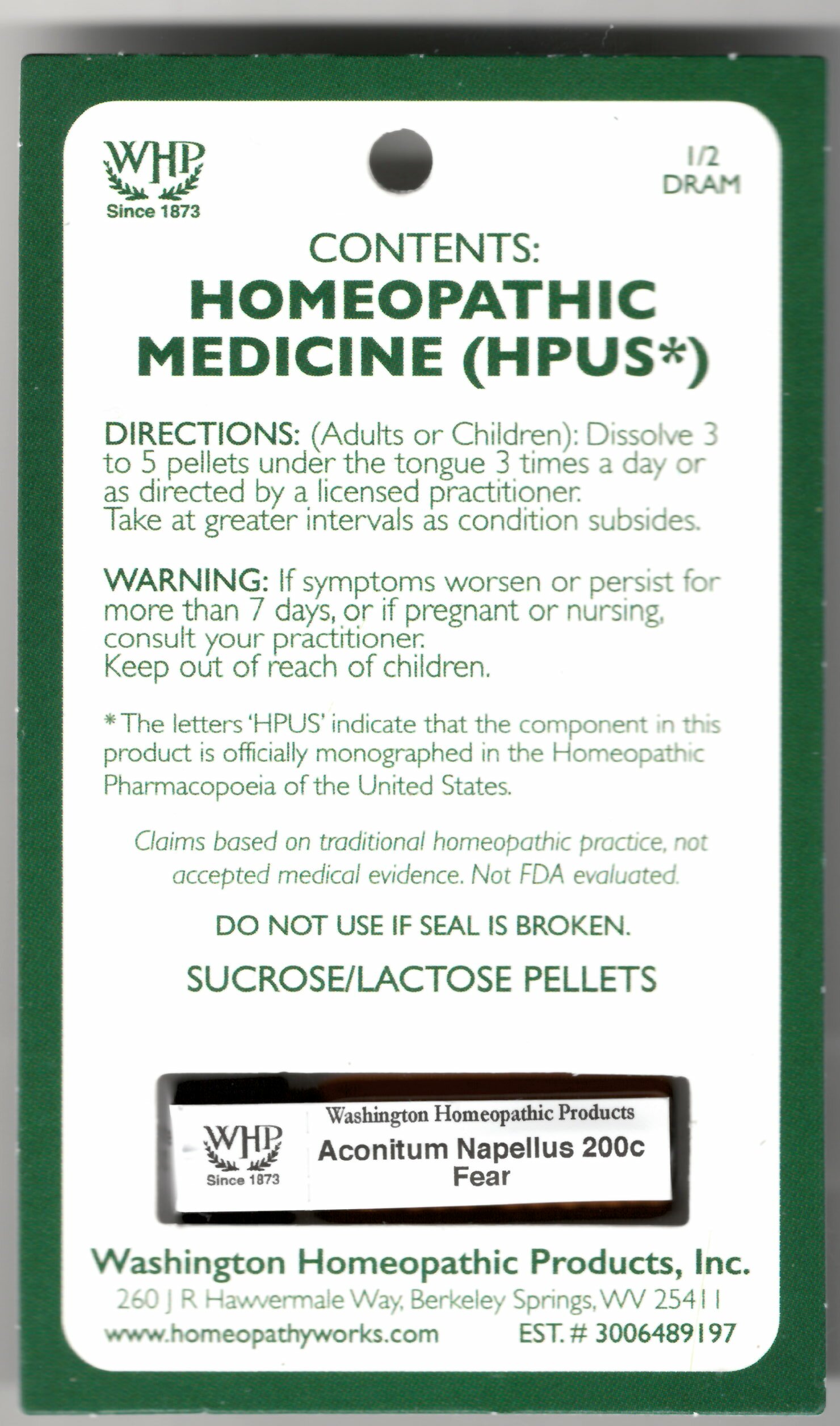 DRUG LABEL: Aconitum Napellus Kit Refill
NDC: 68428-026 | Form: PELLET
Manufacturer: Washington Homeopathic Products
Category: homeopathic | Type: HUMAN OTC DRUG LABEL
Date: 20191211

ACTIVE INGREDIENTS: ACONITUM NAPELLUS 200 [hp_C]/1 1
INACTIVE INGREDIENTS: SUCROSE; LACTOSE

DRUG FACTS

ACTIVE INGREDIENTS

ACONITUM NAPELLUS 200C

USES

To relieve the symptoms of fear.

KEEP OUT OF REACH OF CHILDREN

Keep this and all medicines out of reach of children.

INDICATIONS

ACONITUM NAPELLUS FEAR

STOP USE AND ASK DOCTOR

If symptoms persist/worsen or if pregnant/nursing, stop use and consult your practitioner.

DIRECTIONS

Adults: Dissolve 3 to 5 under the tongue three times a day or as directed by Lic. Practitioner. Take at greater intervals as condition subsides.

Children: Dissolve 3 to 5 under the tongue three times a day or as directed by Lic. Practitioner. Take at greater intervals as condition subsides.

INACTIVE INGREDIENTS

Sucrose/Lactose